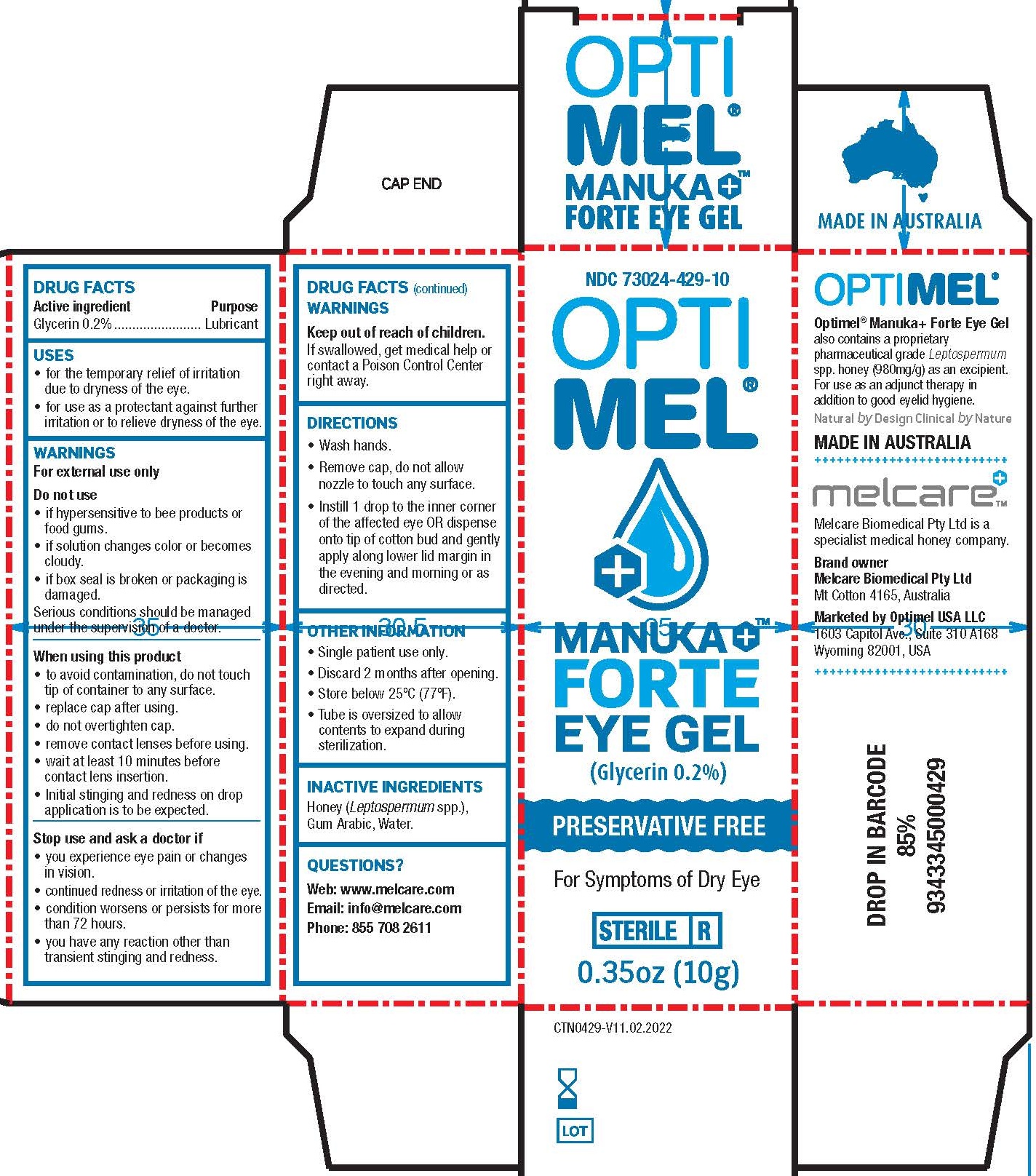 DRUG LABEL: Optimel Manuka Forte Eye Gel
NDC: 73024-429 | Form: GEL
Manufacturer: Melcare Biomedical Pty Ltd
Category: otc | Type: HUMAN OTC DRUG LABEL
Date: 20251209

ACTIVE INGREDIENTS: GLYCERIN 2 mg/1 mL
INACTIVE INGREDIENTS: HONEY; WATER; ACACIA

Optimel Manuka+ Forte Eye Gel

Drug Facts

Active ingredients

Glycerin 0.2%

Purpose

Lubricant

Uses

- for the temporary relief of burning and irritation due to dryness of the eye.
- for use as a protectant against further irritation or to relieve dryness of the eye.

Warnings

For external use only

Do not use

- if hypersensitive to bee products or food gums.
- if solution changes color or becomes cloudy.
- if box seal is broken or packaging is damaged.
- serious conditions should be managed under the supervision of a doctor.

When using this product

- to avoid contamination, do not touch tip of container to any surface.
- replace cap after using.
- do not overtighten cap.
- remove contact lenses before using.
- wait at least 10 minutes before contact lens insertion.
- Initial stinging and redness on drop application is to be expected.

Stop use and ask a doctor if

- you experience eye pain changes in vision
- continued redness or irritation of the eye.
- condition worsens or persists for more than 72 hours.
- you have any reaction other than transient stinging and redness.
- You experience eye pain, change in vision, continued redness or irritation of the eye.
- Condition worsens

Keep out of reach of children.

If swallowed, get medical help or contact a Poison Control Center right away.

Directions

- Wash hands.
- Remove cap, do not allow nozzle to touch any surface.
- Instill 1 drop to the inner corner of the affected OR dispense onto tip of cotton bud and gently apply along lower lid margin up to 3 times daily or as directed.

Other information

- Single patient use only.
- Discard 2 months after opening.
- Store below 25°C (77°F).
- Tube is oversized to allow contents to expand during sterilization.

Inactive ingredients

Honey (Leptospermum spp.), Gum Arabic, Water.

Questions?

Web: www.melcare.com
Email: info@melcare.com
Phone: 8557082611